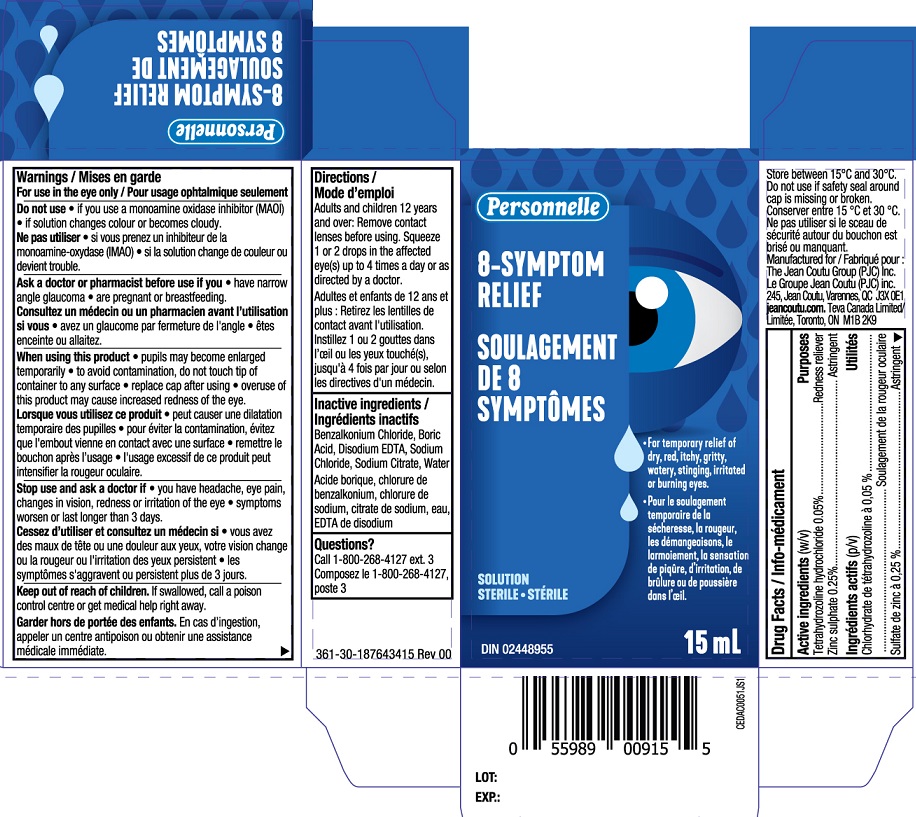 DRUG LABEL: Personnelle 8 Symptom Relief
NDC: 55651-055 | Form: SOLUTION
Manufacturer: KC Pharmaceuticals, Inc.
Category: otc | Type: HUMAN OTC DRUG LABEL
Date: 20251231

ACTIVE INGREDIENTS: TETRAHYDROZOLINE HYDROCHLORIDE 0.05 g/100 mL; ZINC SULFATE 0.25 g/100 mL
INACTIVE INGREDIENTS: BENZALKONIUM CHLORIDE; WATER; EDETATE DISODIUM; SODIUM CHLORIDE; SODIUM CITRATE; BORIC ACID

Personnelle 8-Symptom Relief MFR 15mL